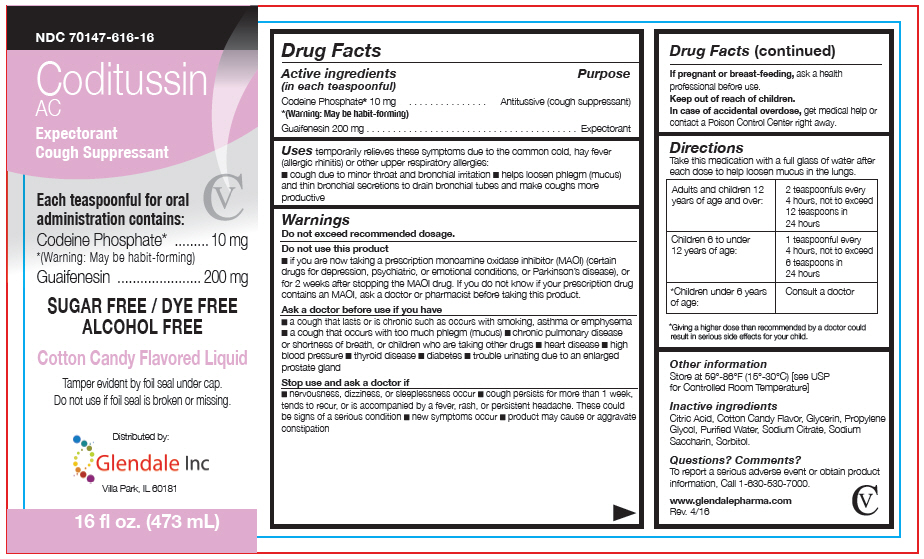 DRUG LABEL: Coditussin AC
NDC: 70147-313 | Form: SYRUP
Manufacturer: Glendale Inc
Category: otc | Type: HUMAN OTC DRUG LABEL
Date: 20160510

ACTIVE INGREDIENTS: CODEINE PHOSPHATE 10 mg/5 mL; GUAIFENESIN 200 mg/5 mL
INACTIVE INGREDIENTS: CITRIC ACID MONOHYDRATE; PROPYLENE GLYCOL; WATER; SACCHARIN SODIUM; SODIUM CITRATE, UNSPECIFIED FORM; SORBITOL; GLYCERIN

Coditussin AC

Drug Facts

ACTIVE INGREDIENT

Active ingredients (in each teaspoonful) | Purpose
Codeine Phosphate [(Warning: May be habit-forming)] 10 mg | Antitussive (cough suppressant)
Guaifenesin 200 mg | Expectorant

Uses

temporarily relieves these symptoms due to the common cold, hay fever (allergic rhinitis) or other upper respiratory allergies:

- cough due to minor throat and bronchial irritation
- helps loosen phlegm (mucus) and thin bronchial secretions to drain bronchial tubes and make coughs more productive

Warnings

Do not exceed recommended dosage.

Do not use this product

- if you are now taking a prescription monoamine oxidase inhibitor (MAOI) (certain drugs for depression, psychiatric, or emotional conditions, or Parkinson's disease), or for 2 weeks after stopping the MAOI drug. If you do not know if your prescription drug contains an MAOI, ask a doctor or pharmacist before taking this product.

Ask a doctor before use if you have

- a cough that lasts or is chronic such as occurs with smoking, asthma or emphysema
- a cough that occurs with too much phlegm (mucus)
- chronic pulmonary disease or shortness of breath, or children who are taking other drugs
- heart disease
- high blood pressure
- thyroid disease
- diabetes
- trouble urinating due to an enlarged prostate gland

Stop use and ask a doctor if

- nervousness, dizziness, or sleeplessness occur
- cough persists for more than 1 week, tends to recur, or is accompanied by a fever, rash, or persistent headache. These could be signs of a serious condition
- new symptoms occur
- product may cause or aggravate constipation

PREGNANCY OR BREAST FEEDING

If pregnant or breast-feeding, ask a health professional before use.

Keep out of reach of children.

In case of accidental overdose, get medical help or contact a Poison Control Center right away.

Directions

Take this medication with a full glass of water after each dose to help loosen mucus in the lungs.

Adults and children 12 years of age and over: | 2 teaspoonfuls every 4 hours, not to exceed 12 teaspoons in 24 hours
Children 6 to under 12 years of age: | 1 teaspoonful every 4 hours, not to exceed 6 teaspoons in 24 hours
[Giving a higher dose than recommended by a doctor could result in serious side effects for your child.] Children under 6 years of age: | Consult a doctor

Other information

Store at 59°-86°F (15°-30°C) [see USP for Controlled Room Temperature]

Inactive ingredients

Citric Acid, Cotton Candy Flavor, Glycerin, Propylene Glycol, Purified Water, Sodium Citrate, Sodium Saccharin, Sorbitol.

Questions? Comments?

To report a serious adverse event or obtain product information, Call 1-630-530-7000.

Distributed by:

Glendale Inc

Villa Park, IL 60181

PRINCIPAL DISPLAY PANEL - 473 mL Bottle Label

NDC 70147-616-16

Coditussin
AC

Expectorant
Cough Suppressant

CV

Each teaspoonful for oral
administration contains:

Codeine Phosphate* 10 mg
*(Warning: May be habit-forming)

Guaifenesin 200 mg

SUGAR FREE / DYE FREE
ALCOHOL FREE

Cotton Candy Flavored Liquid

Tamper evident by foil seal under cap.
Do not use if foil seal is broken or missing.

Distributed by:

Glendale Inc

Villa Park, IL 60181

16 fl oz. (473 mL)